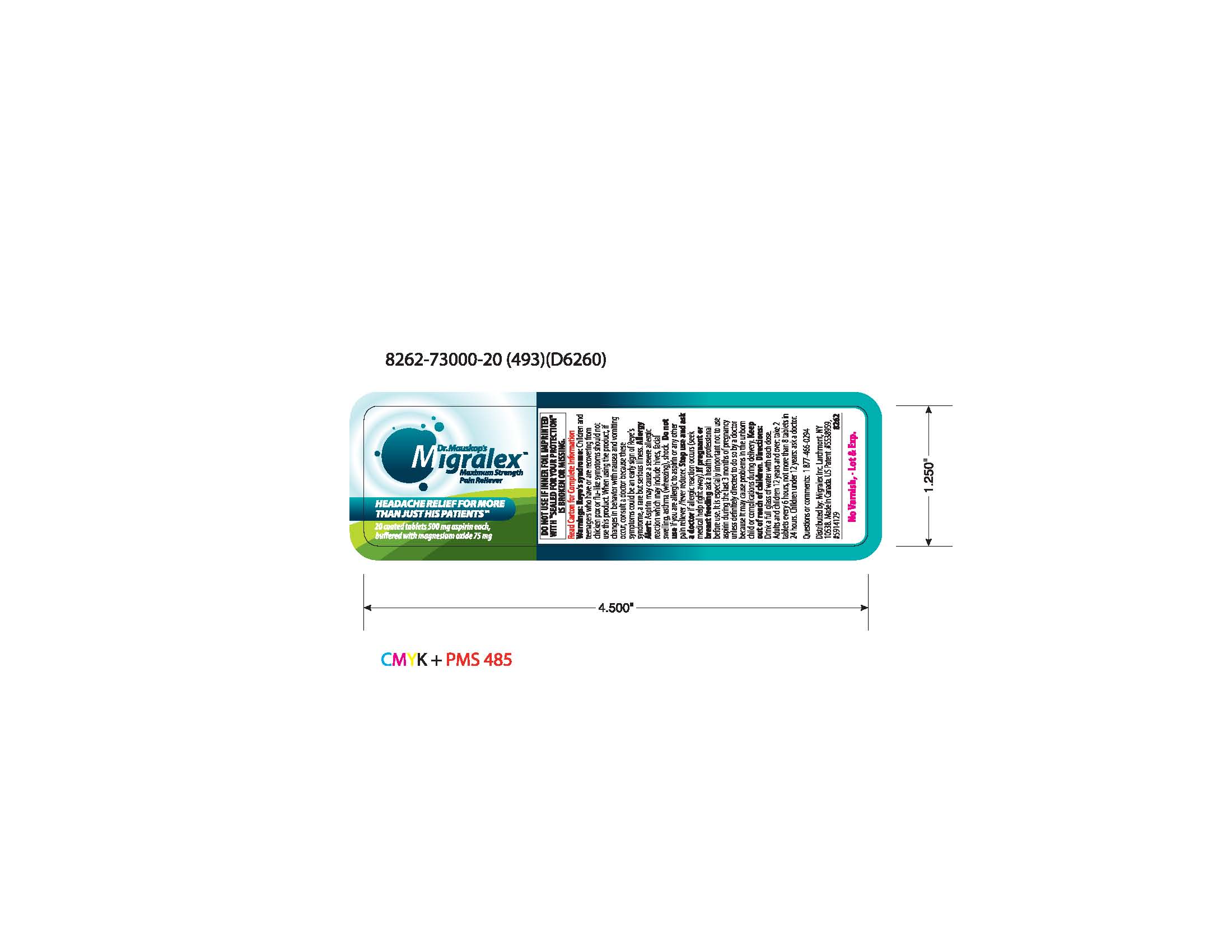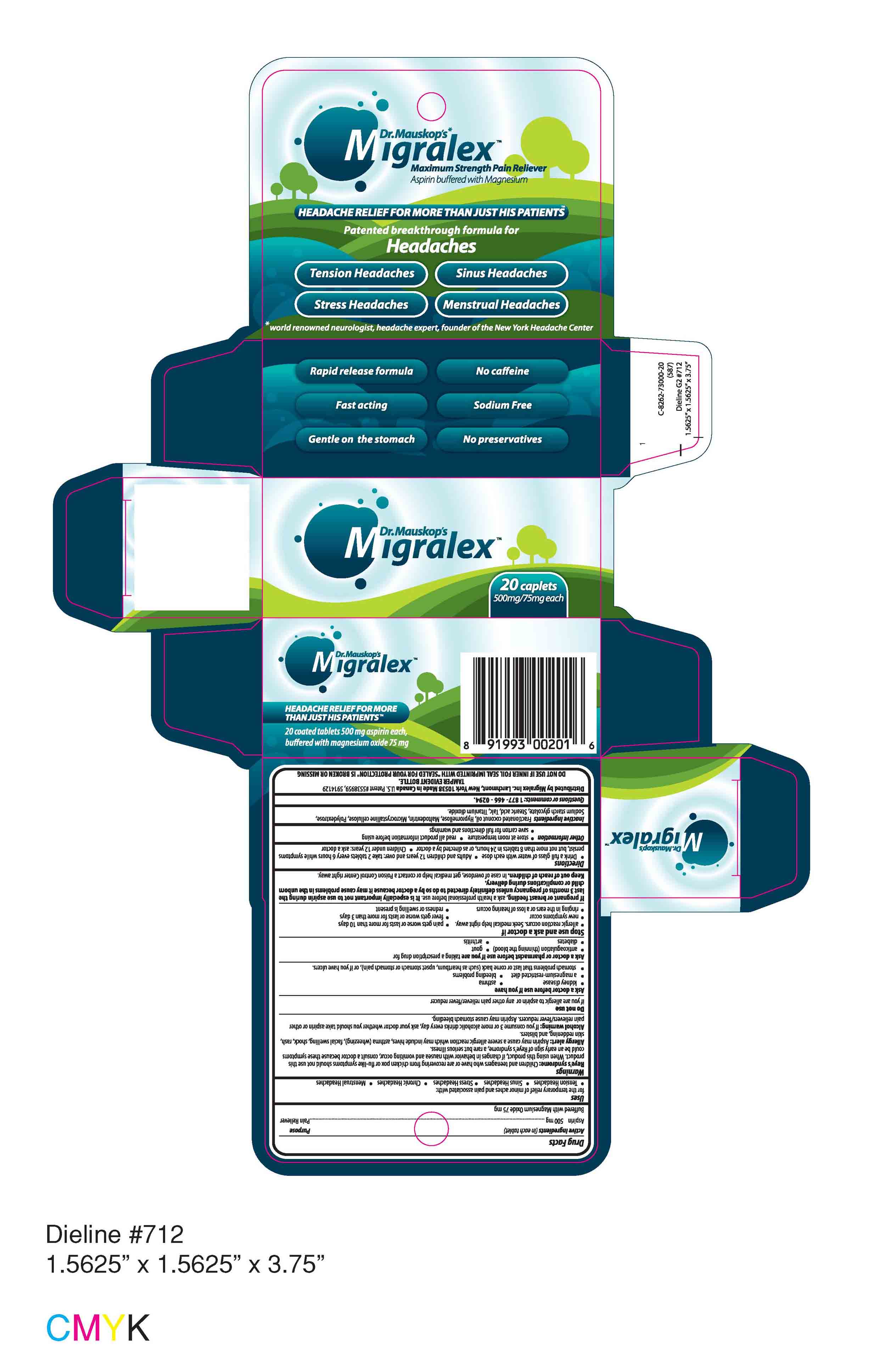 DRUG LABEL: Migralex
NDC: 49886-001 | Form: TABLET, COATED
Manufacturer: Migralex Inc.
Category: otc | Type: HUMAN OTC DRUG LABEL
Date: 20091023

ACTIVE INGREDIENTS: aspirin 500 mg/1 1; magnesium oxide 75 mg/1 1

Migralex Labeling

Active Ingredients (in each tablet)
Aspirin 500 mg (Purpose: Pain Reliever)
Buffered with Magnesium Oxide 75 mg

Uses
for the temporary relief of minor aches and pain associated with:

- Tension Headaches
- Sinus Headaches
- Stress Headaches
- Chronic Headaches
- Menstrual Headaches

Warnings
Reye's syndrome: Children and teenagers who have or are recovering from chicken pox or flu-like symptoms should not use this product. When using this product, if changes in behavior with nausea and vomiting occur, consult a doctor because these symptoms could be an early sign of Reye's syndrome, a rare but serious illness.
Allergy alert: Aspirin may cause a severe allergic reaction which may include hives, asthma (wheezing), facial swelling, shock, rash, skin reddening, and blisters.
Alcohol warning: If you consume 3 or more alcoholic drinks everyday, ask your doctor whether you should take aspirin or other pain relievers/fever reducers. Aspirin may cause stomach bleeding.

Do not use
if you are allergic to aspirin or any other pain reliever/fever reducer

Ask a doctor before use if you have

- kidney disease
- asthma
- a magnesium-restricted diet
- bleeding problems
- stomach problems that last or come back (such as heartburn, upset stomach or stomach pain), or if you have ulcers.

Ask a doctor or pharmacist before use if you are taking a prescription drug for

- anticoagulation (thinning the blood)
- gout
- diabetes
- arthritis

Stop use and ask a doctor if

- allergic reaction occurs. Seek medical help right away.
- pain gets worse or lasts for more than 10 days
- new symptoms occur
- fever gets worse or lasts for more than 3 days
- ringing in the ears or a loss of hearing occurs
- redness or swelling is present

PREGNANCY OR BREAST FEEDING

If pregnant or breast feeding, ask a health professional before use. It is especially important not to use aspirin during the last 3 months of pregnancy unless definitely directed to do so by a doctor because it may cause problems in the unborn child or complications during delivery.

Keep out of reach of children. In case of overdose, get medical help or contact a Poison Control Center right away.

Directions

- Drink a full glass of water with each dose
- Adults and children 12 years and over: take 2 tablets every 6 hours while symptoms persist, but not more than 8 tablets in 24 hours, or as directed by a doctor
- Children under 12 years: ask a doctor

Other Information

- store at room temperature
- read all product information before using
- save carton for full directions and warnings

Inactive Ingredients
Fractionated coconut oil, Hypromellose, Maltodextrin, Microcrystalline cellulose, Polydextrose, Sodium starch glycolate, Stearic acid, Talc, Titanium dioxide.

Questions or comments: 1 877 - 466 - 0294.
Distributed by Migralex Inc. Larchmont, New York 10538 Made in Canada U.S. Patent #5538959, 5914129
TAMPER EVIDENT BOTTLE.
DO NOT USE IF INNER FOIL SEAL IMPRINTED WITH "SEALED FOR YOUR PROTECTION" IS BROKEN OR MISSING